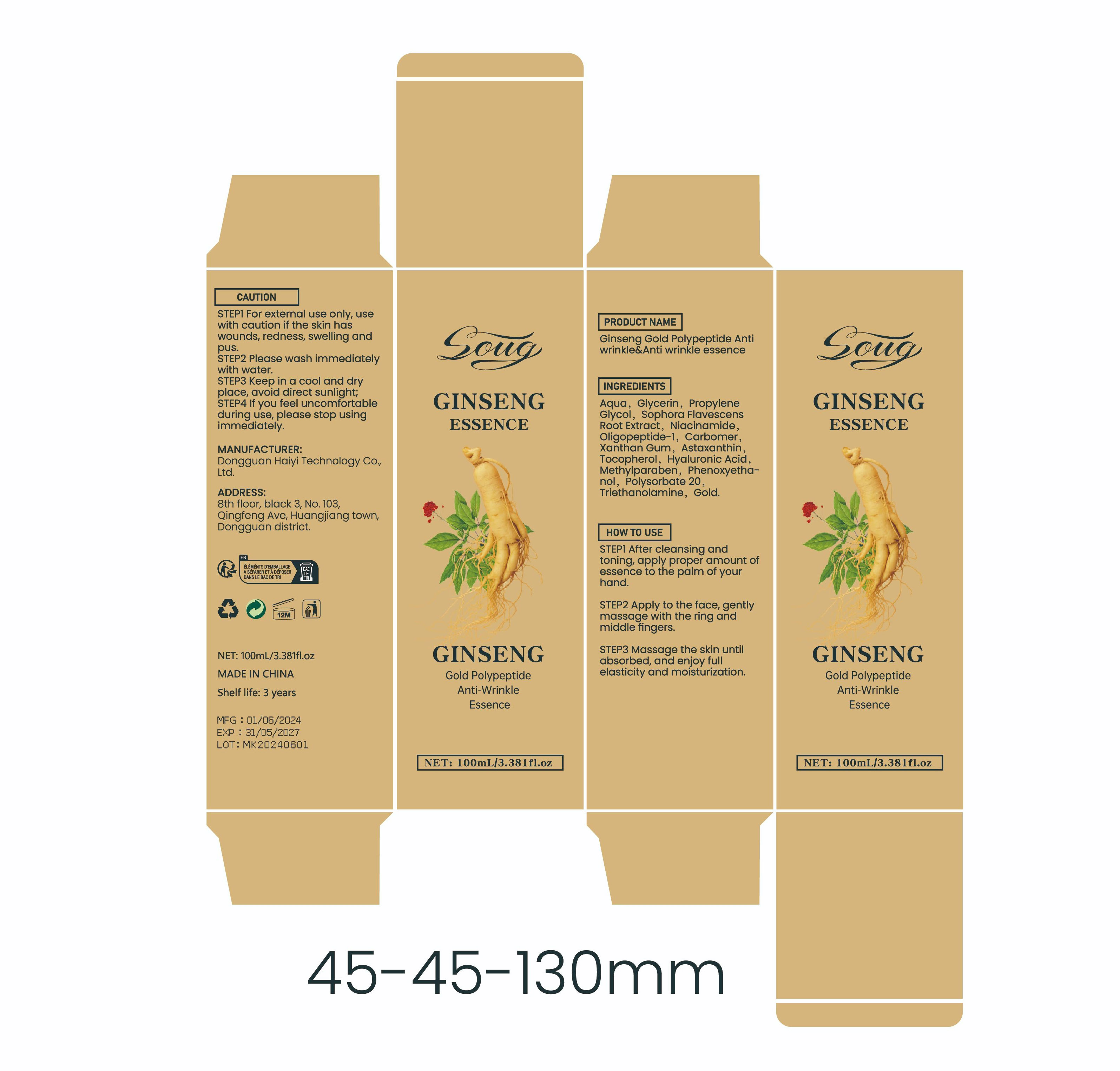 DRUG LABEL: Ginseng Gold Polypeptide Antiwrinkle Anti wrinkle essence
NDC: 84732-031 | Form: LIQUID
Manufacturer: Dongguan Haiyi Technology Co.,Ltd.
Category: otc | Type: HUMAN OTC DRUG LABEL
Date: 20241008

ACTIVE INGREDIENTS: GOLD 1 mg/100 mL
INACTIVE INGREDIENTS: METHYLPARABEN; TROLAMINE; WATER; PROPYLENE GLYCOL; OLIGOPEPTIDE-10; POLYSORBATE 20; XANTHAN GUM; PHENOXYETHANOL; TOCOPHEROL; GLYCERIN; CARBOMER HOMOPOLYMER, UNSPECIFIED TYPE; ASTAXANTHIN; HYALURONIC ACID; SOPHORA FLAVESCENS ROOT; NIACINAMIDE

Active ingredient

Gold

Inactive ingredient

Aqua，Glycerin, Propylene Glycol，Sophora Flavescens Root Extract, Niacinamide.Oligopeptide-l,Carbomer.Xanthan Gum，Astaxanthin，Tocopherol, Hyaluronic Acid.Methylparaben, Phenoxyethanol， Polysorbate 20,Triethanolamine,

Purpose section

Brighten skin tone,Fine lines reduced Moisturize skin.

Warning

STEP1 For external use only, usewith caution if the skin haswounds, redness, swelling andpus.

STEP2 Please wash immediatelywith water.

STEP3 Keep in a cool and dryplace, avoid direct sunlight;

STEP4 lf you feel uncomfortableduring use, please stop usingimmediately.

stop use

This product may cause allergic reactions in asmall number of people.
lf youexperience any discomfort,please stop using it immediately.

not use

Not suitable for use by children, pregnantor breast feeding people.

OUT OF CHILDREN

KEEP THE PRODUCT OUT OF REACH OF CHILDREN to

HOW TO USE

STEP1 After cleansing andtoning, apply proper amount ofessence to the palm of yourhand.
STEP2 Apply to the face, gentlymassage with the ring andmiddle fingers.
STEP3 Massage the skin untilabsorbed, and enjoy fullelasticity and moisturization.

Dosage

take an appropriateamount,Use 2-3 times a week